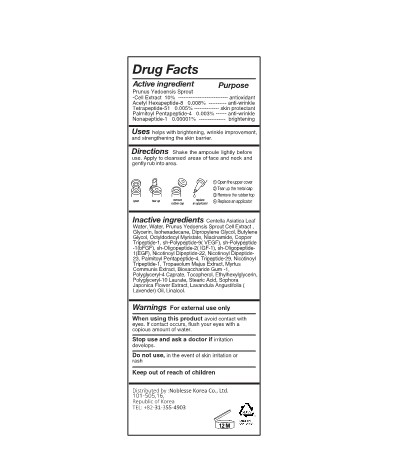 DRUG LABEL: DR.K CELL REPAIR GENIC AMPOULE
NDC: 83153-301 | Form: SOLUTION
Manufacturer: Noblesse Korea Co., Ltd.
Category: otc | Type: HUMAN OTC DRUG LABEL
Date: 20230615

ACTIVE INGREDIENTS: ACETYL HEXAPEPTIDE-8 80.5 g/100 mL; NONAPEPTIDE-1 10 g/100 mL; PALMITOYL PENTAPEPTIDE-4 30 g/100 mL; ALANINE 50 g/100 mL; PRUNUS X YEDOENSIS FLOWER 100 g/100 mL
INACTIVE INGREDIENTS: CENTELLA ASIATICA LEAF; GLYCERYL STEARATE SE; WATER; GLYCERIN; OCTYLDODECYL MYRISTATE; NIACINAMIDE; PREZATIDE COPPER; BASIC FIBROBLAST GROWTH FACTOR (HUMAN); TRIPEPTIDE-29; CENTELLA ASIATICA TRITERPENOIDS; ISOHEXADECANE; HUMAN VASCULAR ENDOTHELIAL GROWTH FACTOR A; BETAINE; ADENOSINE; TROMETHAMINE; GRAPE SEED OIL; BUTYLENE GLYCOL; HUMAN EPIDERMAL GROWTH FACTOR; ANEMARRHENA ASPHODELOIDES ROOT; HIPPOPHAE RHAMNOIDES FRUIT; MECASERMIN; TREMELLA FUCIFORMIS FRUITING BODY; DIOSCOREA JAPONICA ROOT; PANTHENOL; CETOSTEARYL ALCOHOL; 1,2-HEXANEDIOL; DIPROPYLENE GLYCOL; ALMOND OIL; EVENING PRIMROSE OIL; .ALPHA.-BISABOLOL, (+/-)-; MADECASSOSIDE; ARGAN OIL; HYALURONATE SODIUM; ASIATICOSIDE

83153-301 DR.K CELL REPAIR GENIC AMPOULE

Active Ingredients

Prunus Yedoensis Sprout Cell Extract, Acetyl Hexapeptide-8, Tetrapeptide-51, Palmitoyl Pentapeptide-4, Nonapeptide-1

Purposes

helps with brightening, wrinkle improvement, and strengthening the skin barrier.

Uses

Shake the ampoule lightly before use. Apply to cleansed areas of face and neck and gently rub into area.

Warnings

Do not use, in the event of skin irritation or rash

Warnings

Keep out of reach of children

Warnings

Stop use and ask a doctor if irritation develops.

Warnings

When using this product avoid contact with eyes. If contact occurs, flush your eyes with a copious amount of water.

Warnings

For external use only

Directions

Shake the ampoule lightly before use. Apply to cleansed areas of face and neck and gently rub into area.

1. Open the upper cover 2. Tear up the metal cap 3. Remove the rubber top 4. Replace an applicator

Inactive Ingredients

Centella Asiatica Leaf
Water, Water, Prunus Yedoensis Sprout Cell Extract ,
Glycerin, Isohexadecane, Dipropylene Glycol, Butylene
Glycol, Octyldodecyl Myristate, Niacinamide, Acetyl
Hexapeptide-8, Copper Tripeptide-1, sh-Polypeptide-9(
VEGF), sh-Polypeptide-1(bFGF), sh-Oligopeptide-2(
IGF-1), sh-Oligopeptide-1(EGF), Tetrapeptide-51,
Nicotinoyl Dipeptide-22, Nicotinoyl Dipeptide-23,
Palmitoyl Pentapeptide-4, Tripeptide-29, Nicotinoyl
Tripeptide-1, Nonapeptide-1, te, Tropaeolum Majus
Extract, Myrtus Communis Extract, Biosaccharide Gum
-1, Polyglyceryl-4 Caprate, Tocopherol,
Ethylhexylglycerin, Polyglyceryl-10 Laurate, Stearic
Acid, Sophora Japonica Flower Extract, Lavandula
Angustifolia (Lavender) Oil, Linalool.